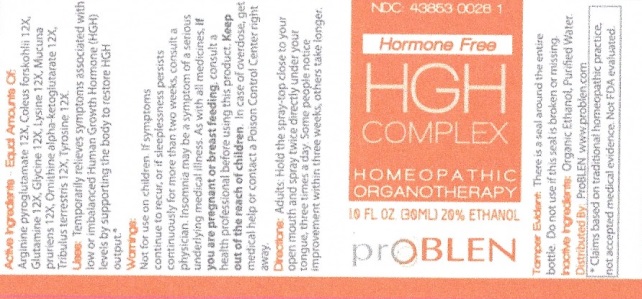 DRUG LABEL: HGH Complex
NDC: 43853-0026 | Form: SPRAY
Manufacturer: ProBlen
Category: homeopathic | Type: HUMAN OTC DRUG LABEL
Date: 20200928

ACTIVE INGREDIENTS: ARGININE PIDOLATE 12 [hp_X]/30 mL; PLECTRANTHUS BARBATUS ROOT 12 [hp_X]/30 mL; GLUTAMINE 12 [hp_X]/30 mL; GLYCINE 12 [hp_X]/30 mL; LYSINE 12 [hp_X]/30 mL; MUCUNA PRURIENS SEED 12 [hp_X]/30 mL; DIORNITHINE OXOGLURATE 12 [hp_X]/30 mL; TRIBULUS TERRESTRIS WHOLE 12 [hp_X]/30 mL; TYROSINE 12 [hp_X]/30 mL
INACTIVE INGREDIENTS: ALCOHOL; WATER

HGH Complex

Active Ingredients - Equal Amounts Of:

Arginine pyroglutamate 12X, Coleus forskohlii 12X, Glutamine 12X, Glycine 12X, Lysine 12X, Mucuna pruriens 12X, Ornithine alpha-ketoglutarate 12X, Tribulus terrestris 12X, Tyrosine 12X

*Claims based on traditional homeopathic practice, not accepted medical evidence. Not FDA evaluated.

INDICATIONS AND USAGE

Uses: Temporarily relieves symtoms associated with low or imbalanced Human Growth Hormone (HGH) levels by supporting the body to restore HGH output.*

Warnings:

Not for use on children. If symptoms continue to recur, or if sleeplessness persists continuously for more than two weeks, consult a physician. Insomnia may be a symptom of a serious underlying medical illness. As with all medicines, if you are pregnant or breast feeding, consult a heatlh professional before using this product. Keep out of reach of children. In case of overdose, get medical or contact a Poison Control Center right away.

Keep out of reach of children.

DOSAGE AND ADMINISTRATION

Directions: Adults: Hold the spray-top close to your open mouth and spray twice directly under your tongue, three times a day. Some people notice improvement within three weeks, others take longer.

OTHER SAFETY INFORMATION

Tamper Evident: There is seal around the entire bottle. Do not use if this seal is broken or missing.

Inactive ingredients: Orangic Ethanol, Purified Water.

QUESTIONS

Distributed By: ProBLEN www.problen.com

PACKAGE LABEL

NDC: 43853-0026-1

Hormone Free

HGH COMPLEX

HOMEOPATHIC

ORGANOTHERAPY

1.0 FL OZ. (30ML) 20% ETHANOL

prOBLEN

PURPOSE

Temporarily relieves symtoms associated with low or imbalanced Human Growth Hormone (HGH) levels by supporting the body to restore HGH output.*